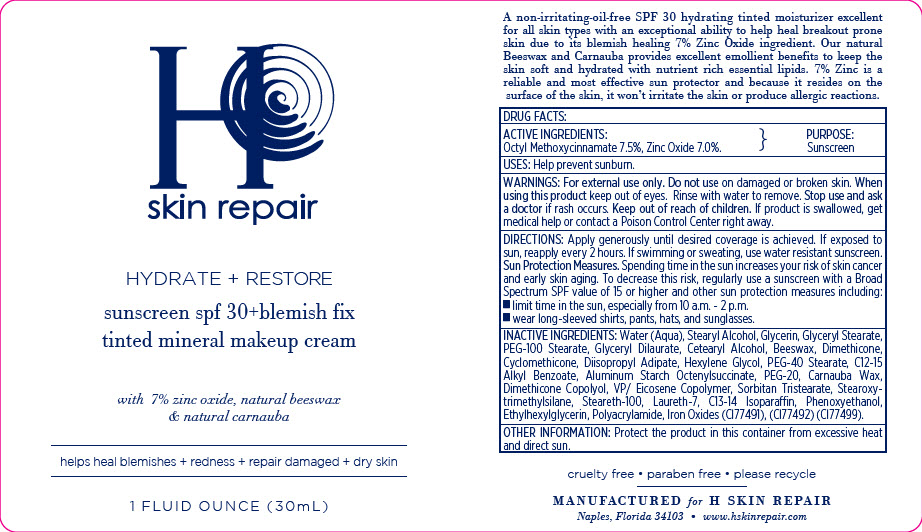 DRUG LABEL: H Skin Repair - Hydrate plus Restore Sunscreen SPF30 plus Blemish Fix Tinted Mineral Makeup
NDC: 66163-7622 | Form: CREAM
Manufacturer: Cosmetic Solutions LLC
Category: otc | Type: HUMAN OTC DRUG LABEL
Date: 20191001

ACTIVE INGREDIENTS: Octinoxate 75 mg/1 mL; Zinc Oxide 70 mg/1 mL
INACTIVE INGREDIENTS: Water; Stearyl Alcohol; Glycerin; Glyceryl Monostearate; PEG-100 Stearate; Glyceryl Dilaurate; Cetostearyl Alcohol; Yellow Wax; Dimethicone; Cyclomethicone; Diisopropyl Adipate; Hexylene Glycol; PEG-40 Stearate; Alkyl (C12-15) Benzoate; Aluminum Starch Octenylsuccinate; POLYETHYLENE GLYCOL 1000; Carnauba Wax; PEG/PPG-18/18 Dimethicone; Sorbitan Tristearate; Stearoxytrimethylsilane; Steareth-100; Laureth-7; C13-14 Isoparaffin; Phenoxyethanol; Ethylhexylglycerin; Ferric Oxide Red; Ferric Oxide Yellow; Ferrosoferric Oxide

H Skin Repair - Hydrate + Restore Sunscreen SPF30 + Blemish Fix Tinted Mineral Makeup Cream

DRUG FACTS:

ACTIVE INGREDIENTS

Octyl Methoxycinnamate 7.5%, Zinc Oxide 7.0%.

PURPOSE

Sunscreen

USES

Help prevent sunburn.

WARNINGS

For external use only. Do not use on damaged or broken skin. When using this product keep out of eyes. Rinse with water to remove. Stop use and ask a doctor if rash occurs.

Keep out of reach of children. If product is swallowed, get medical help or contact a Poison Control Center right away.

DIRECTIONS

Apply generously until desired coverage is achieved. If exposed to sun, reapply every 2 hours. If swimming or sweating, use water resistant sunscreen.

Sun Protection Measures.

Spending time in the sun increases your risk of skin cancer and early skin aging. To decrease this risk, regularly use a sunscreen with a Broad Spectrum SPF value of 15 or higher and other sun protection measures including:

- limit time in the sun, especially from 10 a.m. - 2 p.m.
- wear long-sleeved shirts, pants, hats, and sunglasses.

INACTIVE INGREDIENTS

Water (Aqua), Stearyl Alcohol, Glycerin, Glyceryl Stearate, PEG-100 Stearate, Glyceryl Dilaurate, Cetearyl Alcohol, Beeswax, Dimethicone, Cyclomethicone, Diisopropyl Adipate, Hexylene Glycol, PEG-40 Stearate, C12-15 Alkyl Benzoate, Aluminum Starch Octenylsuccinate, PEG-20, Carnauba Wax, Dimethicone Copolyol, VP/ Eicosene Copolymer, Sorbitan Tristearate, Stearoxytrimethylsilane, Steareth-100, Laureth-7, C13-14 Isoparaffin, Phenoxyethanol, Ethylhexylglycerin, Polyacrylamide, Iron Oxides (Cl77491), (Cl77492) (Cl77499).

OTHER INFORMATION

Protect the product in this container from excessive heat and direct sun.

PRINCIPAL DISPLAY PANEL - 30 mL Bottle Label

H
skin repair

HYDRATE + RESTORE

sunscreen spf 30+blemish fix
tinted mineral makeup cream

with 7% zinc oxide, natural beeswax
& natural carnauba

helps heal blemishes + redness + repair damaged + dry skin

1 FLUID OUNCE (30mL)